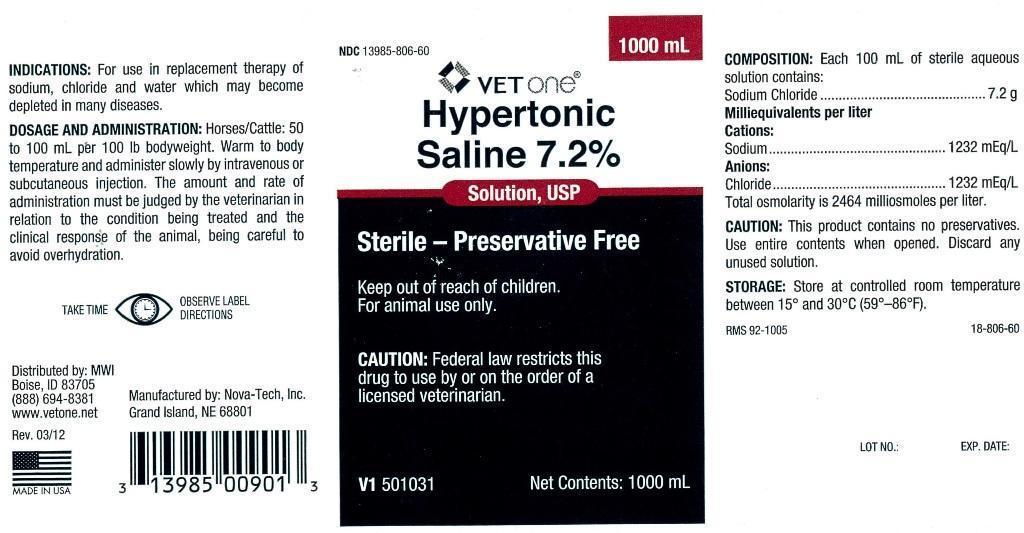 DRUG LABEL: Hypertonic Saline
NDC: 13985-806 | Form: INJECTION, SOLUTION
Manufacturer: MWI (VetOne)
Category: animal | Type: PRESCRIPTION ANIMAL DRUG LABEL
Date: 20140604

ACTIVE INGREDIENTS: SODIUM CHLORIDE 7.2 g/100 mL

Hypertonic Saline 7.2%

INDICATIONS:

For use in replacement therapy of sodium, chloride and water which may become depleted in many diseases.

DOSAGE AND ADMINISTRATION:

Horses/Cattle: 50 to 100 mL per 100 lb bodyweight. Warm to body temperature and administer slowly by intravenous or subcutaneous injection. The amount and rate of administration must be judged by the veterinarian in relation to the condition being treated and the clinical response of the animal, being careful to avoid overhydration.

PRECAUTIONS

TAKE TIME OBSERVE LABEL DIRECTIONS

INFORMATION FOR OWNERS/CAREGIVERS

Distributed by: MWI
Boise, ID 83705
(888) 694-8381
www.vetone.net

Manufactured by: Nova-Tech, Inc.
Grand Island, NE 68801

Rev. 03/12

Solution, USP

Sterile-Preservative Free

V1 501031

Net Contents: 1000 mL

RMS 92-1005 18-806-60

LOT NO.: EXP. DATE:

Keep out of reach of children.

VETERINARY INDICATIONS

For animal use only.

CAUTION:

Federal law restricts this drug to use by or on the order of a licensed veterinarian.

COMPOSITION:

Each 100 mL of sterile aqueous solution contains:
Sodium Chloride........................7.2 g
Milliequivalents per liter
Cations:
Sodium.................................1232 mEq/L
Anions:
Chloride................................1232 mWq/L
Total osmolarity is 2464 millosmoles per liter.

CAUTION:

This product contains no preservatives. Use entire contents when opened. Discard any unused solution.

STORAGE:

Store at controlled room temperature between 15 degrees and 30 degrees C (59 degrees - 86 degrees F).